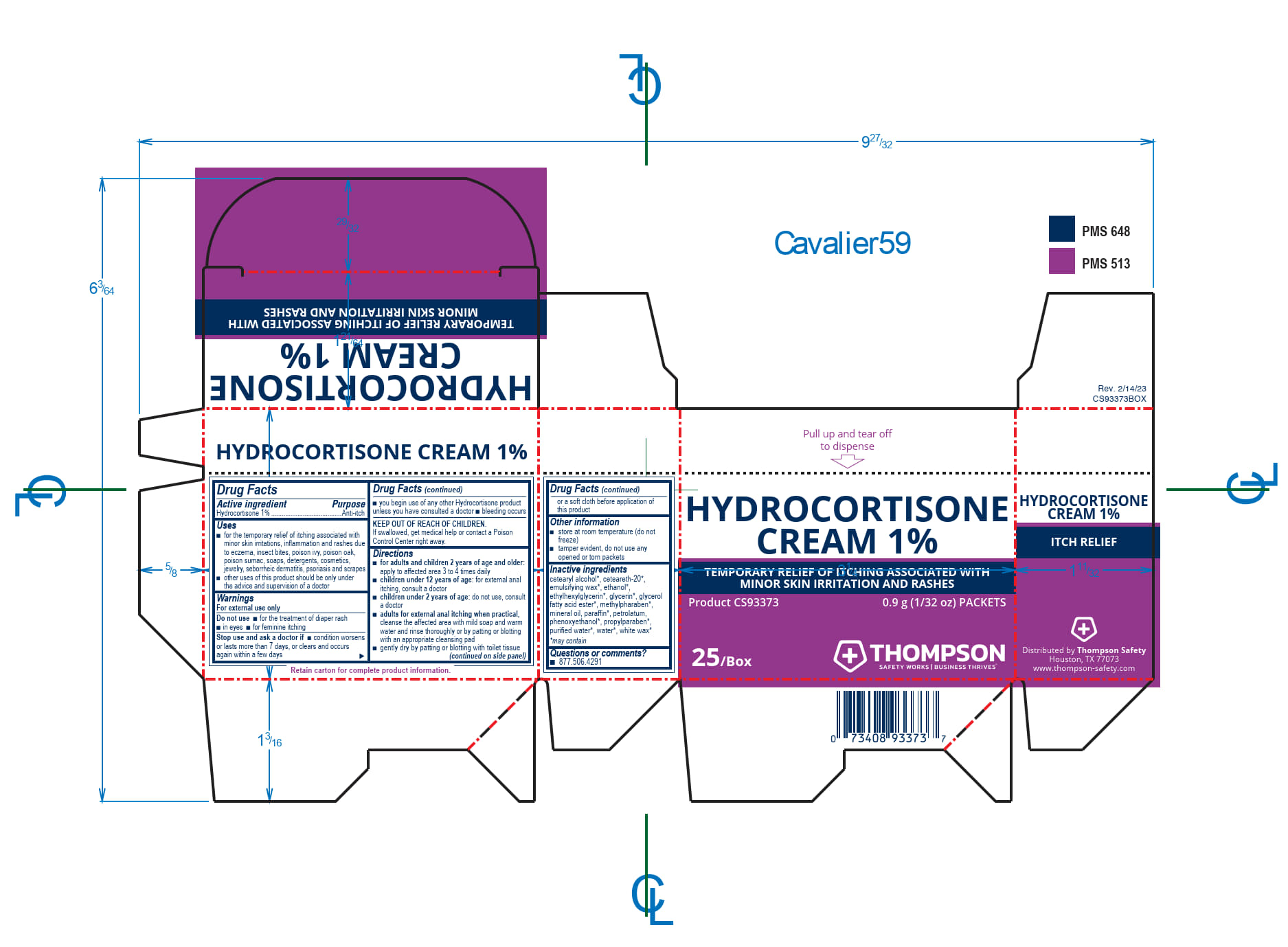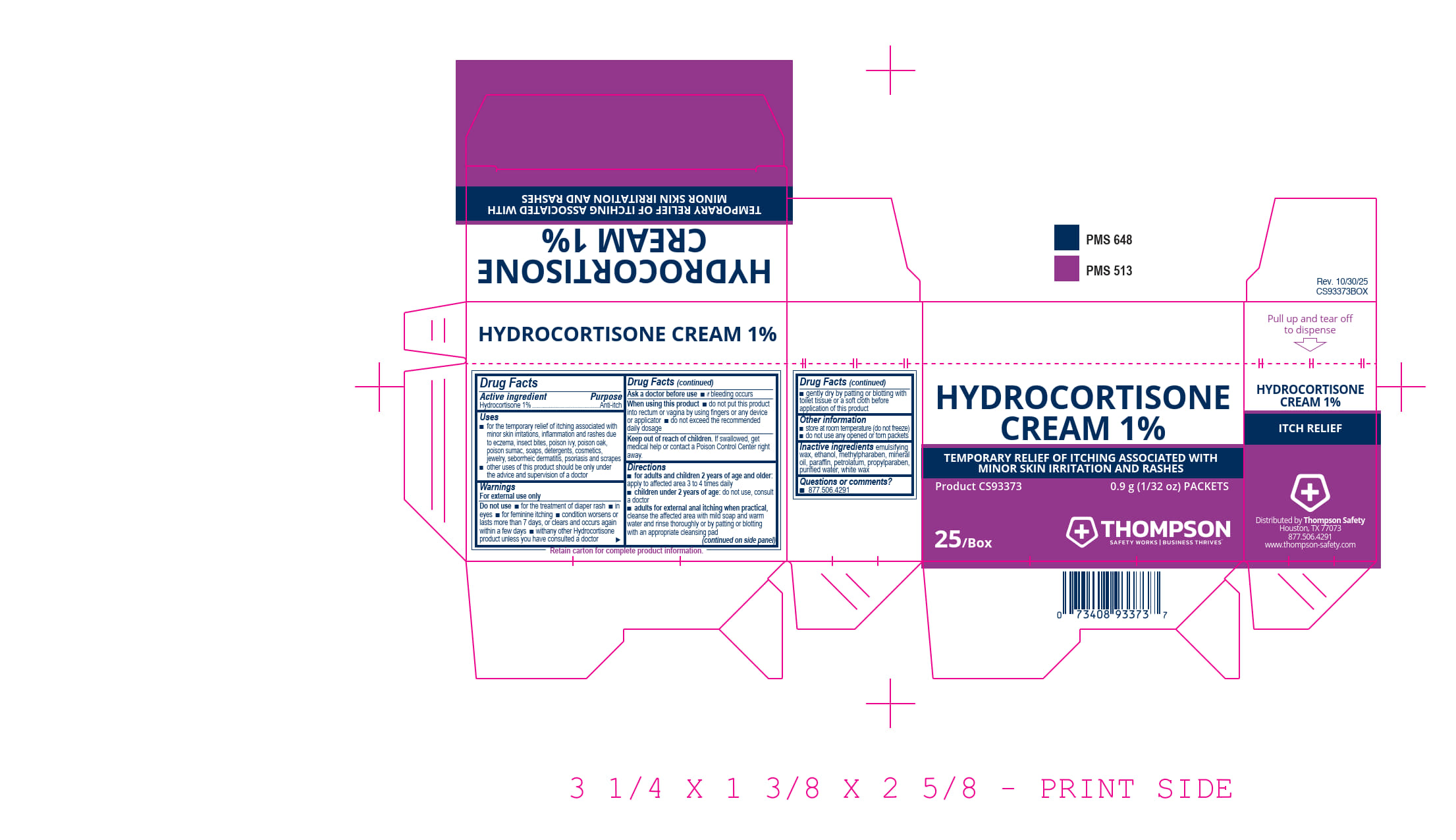 DRUG LABEL: Thompson Hydrocortisone 1%
NDC: 73408-937 | Form: CREAM
Manufacturer: Thompson
Category: otc | Type: HUMAN OTC DRUG LABEL
Date: 20251205

ACTIVE INGREDIENTS: HYDROCORTISONE 10 mg/1 g
INACTIVE INGREDIENTS: ALCOHOL; METHYLPARABEN; PROPYLPARABEN; MINERAL OIL; PARAFFIN; PETROLATUM; WATER; WHITE WAX

Thompson Hydrocortisone Cream 1%

Drug Facts

Active ingredient

Hydrocortisone 1%

PURPOSE

Purose

Anti-itch

Uses

- for the temporary relief of itching associated with minor skin irritations and rashes due to eczema, insect bites, poison ivy, poison oak, poison sumac, soaps, detergents, cosmetics, jewlry, seborrheic dermatitis, psoriasis and scrapes
- other uses of this product should be only under the advice and supervision of a doctor

Warnings

For external use only

Do not use

- for the treatment of diaper rash
- in eyes
- for feminine itching

Stop use and ask a doctor if

- condition worsens or lasts more than 7 days, or clears and occurs again within a few days
- you begin use of any other Hydrocortisone product unless you have consulted a doctor
- bleeding occurs

KEEP OUT OF REACH OF CHILDREN.

If swallowed, get medical help or contact a Poison Control Center right away.

Directions

- for adults and children 2 years of age and older: apply to the affected area 3 to 4 times daily
- children under 12 years of age: for external anal itching, consult a doctor
- children under 2 years of age: do not use, consult a doctor
- adults for external anal itching when practical, cleanse the affected area with mild soap and warm water and rinse thoroughly or by patting or blotting with appropriate cleansing pad
- gently dry by patting or blotting with toilet tissue or a soft cloth before application of this product

Other information

- store at room temperature (do not freeze)
- tamper evident. do not use any opened or torn packets

Inactive ingredients

cetearyl alcohol*, ceteareth-20*, emulsifying wax*, ethanol*, ethylhexylglycerin*, glycerin*, glyceryl fatty acid ester*, methylpharaben*, mineral oil, paraffin*, petrolatum, phenoxyethanol*, propylparaben*, purified water, water*, white wax*

*may contain

Questions or comments? 877.506.4291

PACKAGE LABEL

Pull up and tear off to dispense

Hydrocortisone Cream 1%

Temporary Relief of Itching Associated with

Minor Skin Irritation and Rashes

Product CS93373 0.9 g (1/32 oz) Packets

25/Box

THOMPSON

Safety Works | Business Thrives™